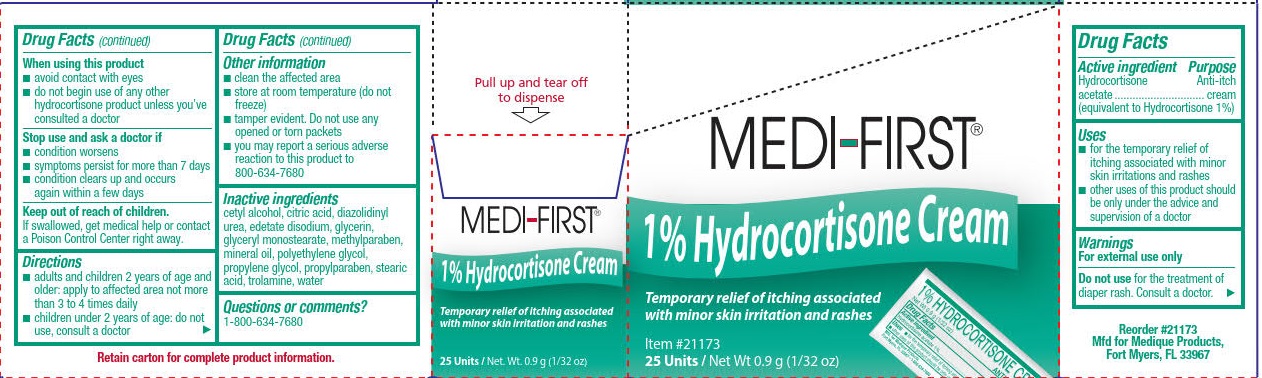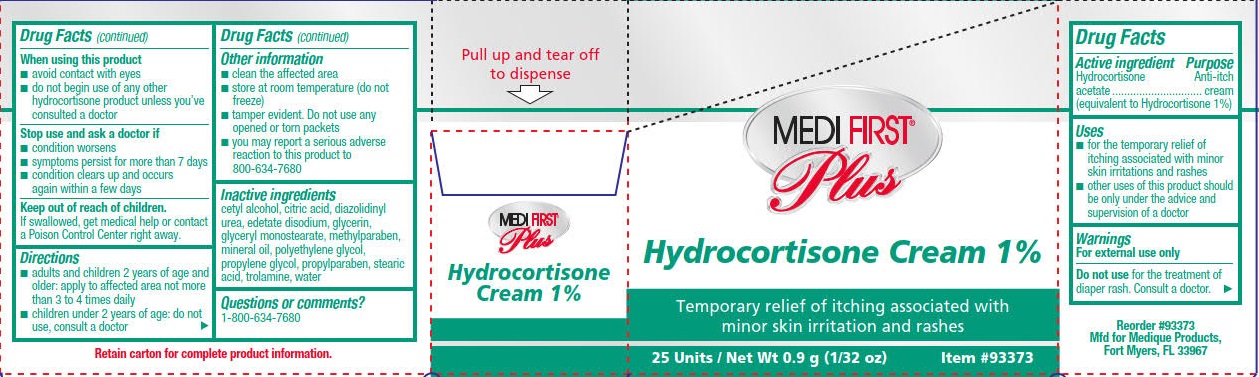 DRUG LABEL: Medi-First Hydrocortisone 1%
NDC: 47682-207 | Form: CREAM
Manufacturer: Unifirst First Aid Corporation
Category: otc | Type: HUMAN OTC DRUG LABEL
Date: 20240117

ACTIVE INGREDIENTS: HYDROCORTISONE ACETATE 10 mg/1 g
INACTIVE INGREDIENTS: GLYCERIN; PROPYLPARABEN; STEARIC ACID; TROLAMINE; CITRIC ACID MONOHYDRATE; DIAZOLIDINYL UREA; METHYLPARABEN; POLYETHYLENE GLYCOL, UNSPECIFIED; WATER; EDETATE DISODIUM; GLYCERYL MONOSTEARATE; MINERAL OIL; CETYL ALCOHOL; PROPYLENE GLYCOL

Medi-First 1% Hydrocortisone Cream

Drug Facts

Active ingredient

Hydrocortisone acetate (equivalent to Hydrocorisone 1%)

Purpose

Anti-itch cream

Uses

- for the temporary relief of itching associated with minor skin irritations and rashes
- other uses of this product should be only under the advice and supervision of a doctor

Warnings

For external use only.

Do not use for the treatment of diaper rash. Consult a doctor.

When using this product

- avoid contact with eyes
- do not begin use of any other hydrocortisone product unless you've consulted a doctor

Stop use and ask a doctor if

- condition worsens
- symptoms persist for more than 7 days
- condition clears up and occurs again within a few days

Keep out of reach of children.

If swallowed, get medical help or contact a Poison Control Center right away.

Directions

- adults and children 2 years of age and older: apply to the affected area not more than 3 to 4 times daily
- children under 2 years of age: do not use, consult a doctor

Other information

- clean the affected area
- store at room temperature (do not freeze)
- tamper evident. Do not use any opened or torn packets
- you may reportr a serioud adverse reaction to this product to 800-634-7680

Inactive ingredients

cetyl alcohol, citric acid, diazolidinyl urea, edetate disodium, glycerin, glyceryl monostearate, methylparaben, mineral oil, polyethylene glycol, propylene glycol, propylparaben, stearic acid, trolamine, water

Questions or comments? 1-800-634-7680

PACKAGE LABEL

Medi-First®

1% Hydrocortisone Cream

Temporary relief of itching associated with minor skin irritation and rashes

Item #21173

0.9 g (1/32 oz)

Packets - 25 per box

PACKAGE LABEL

Medi-First® Plus

Hydrocortisone Cream 1%

Temporary relief of itching associated with minor skin irritations and rashes

25 Units/Net Wt 0.9 g (1/32 oz)